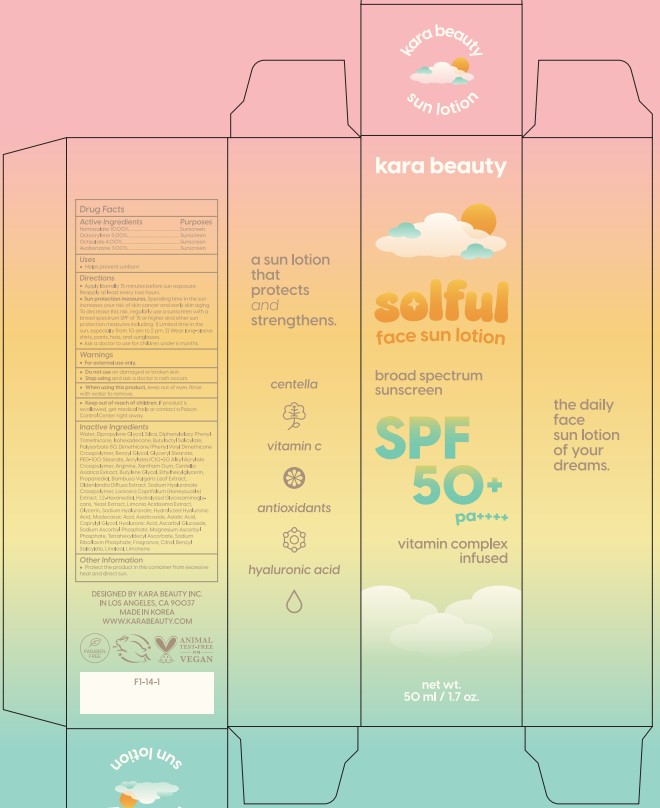 DRUG LABEL: solful face sunlotion
NDC: 83918-001 | Form: LOTION
Manufacturer: KARA BEAUTY INC
Category: otc | Type: HUMAN OTC DRUG LABEL
Date: 20231228

ACTIVE INGREDIENTS: HOMOSALATE 100 mg/1 mL; OCTOCRYLENE 50 mg/1 mL; OCTISALATE 40 mg/1 mL; AVOBENZONE 30 mg/1 mL
INACTIVE INGREDIENTS: WATER; DIPROPYLENE GLYCOL; SILICON DIOXIDE; DIPHENYLSILOXY PHENYL TRIMETHICONE; ISOHEXADECANE; BUTYLOCTYL SALICYLATE; POLYSORBATE 80; DIMETHICONE/PHENYL VINYL DIMETHICONE CROSSPOLYMER; ETHYLENE GLYCOL MONOBENZYL ETHER; GLYCERYL MONOSTEARATE; PEG-100 STEARATE; ACRYLATES/C10-30 ALKYL ACRYLATE CROSSPOLYMER (60000 MPA.S); ARGININE; XANTHAN GUM; CENTELLA ASIATICA TRITERPENOIDS; BUTYLENE GLYCOL; ETHYLHEXYLGLYCERIN; PROPANEDIOL; BAMBUSA VULGARIS LEAF; SCLEROMITRION DIFFUSUM WHOLE; PEG-9 DIGLYCIDYL ETHER/SODIUM HYALURONATE CROSSPOLYMER; LONICERA CAPRIFOLIUM FLOWER; 1,2-HEXANEDIOL; HYDROLYZED GLYCOSAMINOGLYCANS (BOVINE; 50000 MW); YEAST, UNSPECIFIED; LIMONIA ACIDISSIMA WHOLE; GLYCERIN; HYALURONATE SODIUM; MADECASSIC ACID; ASIATICOSIDE; ASIATIC ACID; CAPRYLYL GLYCOL; HYALURONIC ACID; ASCORBYL GLUCOSIDE; SODIUM ASCORBYL PHOSPHATE; MAGNESIUM ASCORBYL PHOSPHATE; TETRAHEXYLDECYL ASCORBATE; RIBOFLAVIN 5'-PHOSPHATE SODIUM ANHYDROUS; CITRAL; BENZYL SALICYLATE; LINALOOL, (+/-)-; LIMONENE, (+)-

83918-001_solful face sun lotion

PURPOSE

Sunscreen

ACTIVE INGREDIENT

Homosalate 10%, Octocrylene 5%, Octisalate 4%, Avobenzone 3%

INDICATIONS AND USAGE

Helps prevent sunburn

DOSAGE AND ADMINISTRATION

Apply liberally 15 minutes before sun exposure. Reapply at least every two hours
Sun protection measures. Spending time in the sun increases your risk of skin cancer and early skin aging. To decrease this risk, regularly use a sunscreen with a broad spectrum SPF of 15 of higher and other sun protection measures including: 1) Limited time in the sun, especially from 10 am to 2 pm. 2) Wear long-sleeve shirts, pants, hats, and sunglasses
Ask a doctor to use for children under 6 months

WARNINGS

For external use only.

Do not use on damaged or broken skin

When using this product, keep out of eyes. Rinse with water to remove.

Stop using and ask a doctor if rash occurs.

KEEP OUT OF REACH OF CHILDREN

Keep out of reach of the children. If product is swallowed, get medical help or contact a poison control center right away.

INACTIVE INGREDIENT

Water, Dipropylene Glycol, Silica, Diphenylsiloxy Phenyl Trimethicone, Isohexadecane, Butyloctyl Salicylate, Polysorbate 80, Dimethicone/Phenyl Vinyl Dimethicone Crosspolymer, Benzyl Glycol, Glyceryl Stearate, PEG-100 Stearate, Acrylates/C10-30 Alkyl Acrylate Crosspolymer, Arginine, Xanthan Gum, Centella Asiatica Extract, Butylene Glycol, Ethylhexylglycerin, Propanediol, Bambusa Vulgaris Leaf Extract, Oldenlandia Diffusa Extract, Sodium Hyaluronate Crosspolymer, Lonicera Caprifolium (Honeysuckle) Extract, 1,2-Hexanediol, Hydrolyzed Glycosaminoglycans, Yeast Extract, Limonia Acidissima Extract, Glycerin, Sodium Hyaluronate, Hydrolyzed Hyaluronic Acid, Madecassic Acid, Asiaticoside, Asiatic Acid, Caprylyl Glycol, Hyaluronic Acid, Ascorbyl Glucoside, Sodium Ascorbyl Phosphate, Magnesium Ascorbyl Phosphate, Tetrahexyldecyl Ascorbate, Sodium Riboflavin Phosphate, Fragrance, Citral, Benzyl Salicylate, Linalool, Limonene

OTHER SAFETY INFORMATION

Protect the product in the container from excessive heat and direct sun